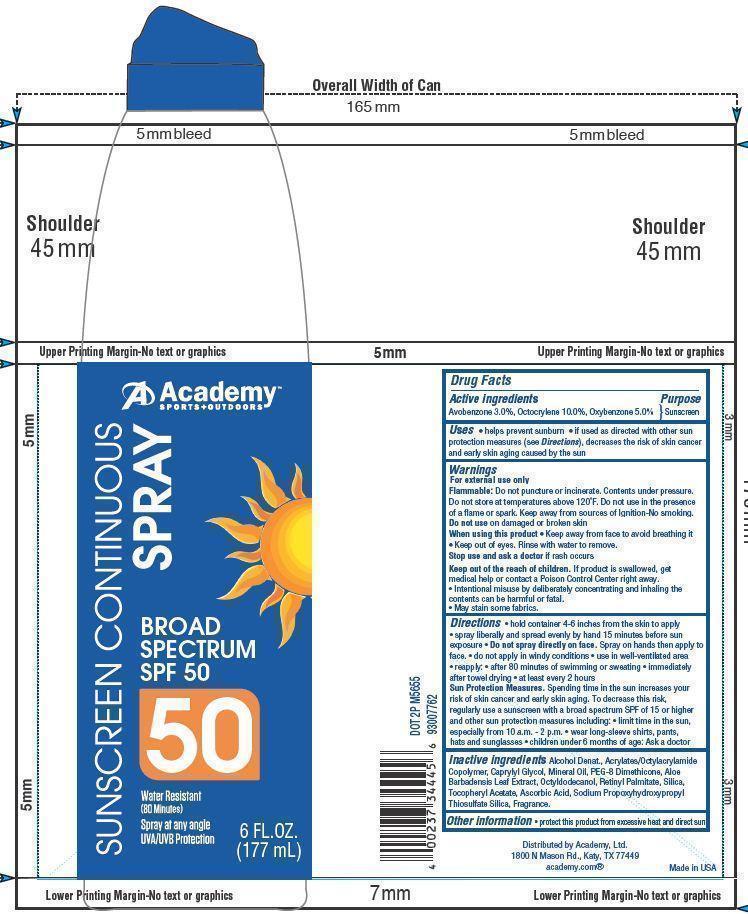 DRUG LABEL: Academy Continuous
NDC: 59054-140 | Form: SPRAY
Manufacturer: ACADEMY, LTD
Category: otc | Type: HUMAN OTC DRUG LABEL
Date: 20130830

ACTIVE INGREDIENTS: AVOBENZONE 3 g/100 g; OCTOCRYLENE 10 g/100 g; OXYBENZONE 5 g/100 g
INACTIVE INGREDIENTS: CAPRYLYL GLYCOL; MINERAL OIL; ALOE VERA LEAF; OCTYLDODECANOL; VITAMIN A PALMITATE; SILICON DIOXIDE; .ALPHA.-TOCOPHEROL ACETATE; ASCORBIC ACID

Drug Facts

Active Ingredients

Avobenzone 3.0

Octocrylene 10.0

Oxybenzone 5.0

Purpose

Sunscreen

Uses

- Helps prevent sunburn
- If used as directed with other sun protection measures (see Directions), decrease the risk of skin cancer and early skin aging caused by the sun.

Warnings

For external use only.

Flammable:Do not puncture or incinerate. Contents under pressure. Do not store at temperature above 120 ^0F. Do not use in the flame or spark. Keep away from sources of ignition. No smoking.

Do not use on damaged or broken skin.

When using this product

- Keep away from face to avoid breathing it.
- Keep out of eyes. Rinse with water to remove.

Stop use and ask a doctor

if rash occurs

Keep out of reach of children

If swallowed, get medical help or contact a Poison Control Center right away.

- May stain some fabrics.
- Intentional misuse by deliberately concentrating and inhaling the contents can be harmful or fatal.

Directions

- hold container 4-6 inches from the skin to apply
- spray liberally and spread evenly by hand 15 minutes before sun exposure
- Do not spray directly on face. Spray on hands and then apply to face
- do not apply in windy conditions
- use in well ventilated area
- reapply
- after 80 minutes of swimming or sweating
- immediately after towel drying
- at least every 2 hours
- Sun Protection Measures: Spending time in the sun increases your risk of skin cancer and early skin aging. To decrease this risk, regularly use a sunscreen with a broad spectrum SPF of 15 or higher and other sun protection measures including:
- limit time in the sun, especially from 10 a.m. - 2 p.m.
- wear long-sleeve shirts, pants, hats and sunglasses
- children under 6 months of age: Ask a doctor

Inactive ingredients

Alcohol Denat., Acrylates/Octylacrylamide Copolymer, Caprylyl Glycol, Mineral Oil, PEG-8 Dimethicone, Aloe Barbadensis Leaf Extract, Octyldodecanol, Retinyl Palmitate, Silica, Tocopheryl Acetate, Ascorbic Acid, Sodium Propoxyhydroxypropyl Thiosulfate Silica, Fragrance

Principal Display Panel

Academy

SPORTS+OUTDOORS

SUNSCREEN CONTINUOUS

SPRAY

BROAD SPECTRUM SPF 50

50

Water Resistant (80 Minutes)

Spray at any angle

UVA/UVB Protection

6 FL.OZ. (177 mL)

Other information

- protect this product from excessive heat and direct sun